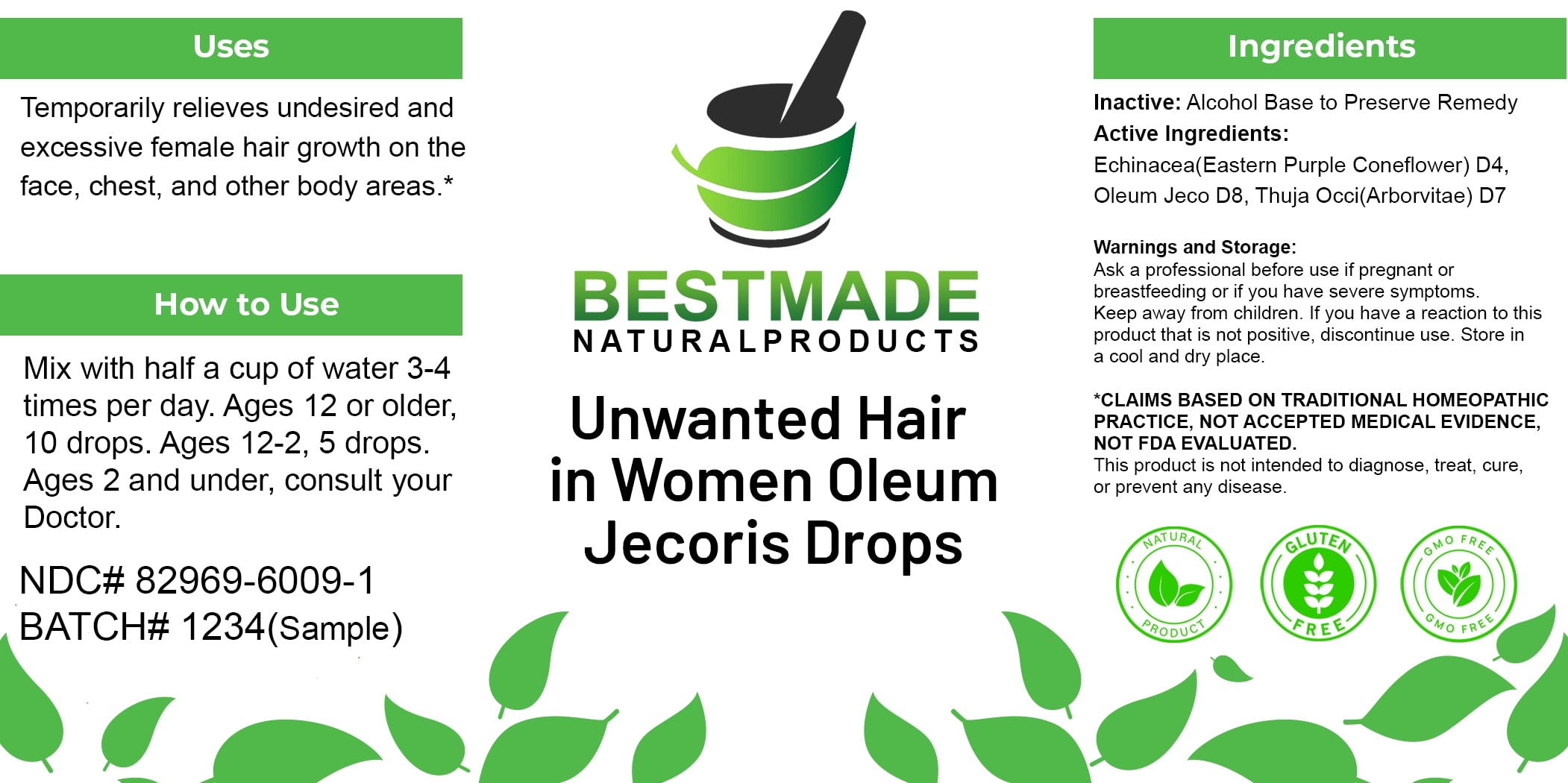 DRUG LABEL: Bestmade Natural Products Unwanted Hair in Women Oleum Jecoris Drops
NDC: 82969-6009 | Form: LIQUID
Manufacturer: Bestmade Natural Products
Category: homeopathic | Type: HUMAN OTC DRUG LABEL
Date: 20250314

ACTIVE INGREDIENTS: COD LIVER OIL 30 [hp_C]/30 [hp_C]; THUJA OCCIDENTALIS LEAFY TWIG 30 [hp_C]/30 [hp_C]; ECHINACEA, UNSPECIFIED 30 [hp_C]/30 [hp_C]
INACTIVE INGREDIENTS: ALCOHOL 30 [hp_C]/30 [hp_C]

Unwanted Hair in Women Oleum Jecoris Drops

DOSAGE AND ADMINISTRATION

How to Use

Mix with half a cup of water 3-4 times per day. Ages 12 or older, 10 drops. Ages 12-2, 5 drops. Ages 2 and under, consult your Doctor.

Inactive:

Alcohol Base to Preserve Product

Uses

Temporarily relieves undesired and excessive female hair growth on the face, chest, and other body areas.*

*CLAIMS BASED ON TRADITIONAL HOMEOPATHIC PRACTICE, NOT ACCEPTED MEDICAL EVIDENCE, NOT FDA EVALUATED.

This product is not intended to diagnose, treat, cure, or prevent any disease.

Uses

Temporarily relieves undesired and excessive female hair growth on the face, chest, and other body areas.*

*CLAIMS BASED ON TRADITIONAL HOMEOPATHIC PRACTICE, NOT ACCEPTED MEDICAL EVIDENCE, NOT FDA EVALUATED.

This product is not intended to diagnose, treat, cure, or prevent any disease.

Active Ingredients:
Echinacea(Eastern Purple Coneflower) D4, Oleum Jeco D8, Thuja Occi(Arborvitae) D7

KEEP OUT OF REACH OF CHILDREN

Warnings and Storage:

Ask a professional before use if pregnant or breastfeeding or if you have severe symptoms. Keep away from children. If you have a reaction to this product that is not positive, discontinue use. Store in a cool and dry place.

Warnings and Storage:

Ask a professional before use if pregnant or breastfeeding or if you have severe symptoms. Keep away from children. If you have a reaction to this product that is not positive, discontinue use. Store in a cool and dry place.

*CLAIMS BASED ON TRADITIONAL HOMEOPATHIC PRACTICE, NOT ACCEPTED MEDICAL EVIDENCE NOT FDA EVALUATED.

This product is not intended to diagnose, treat, cure, or prevent any disease.

Entire package label